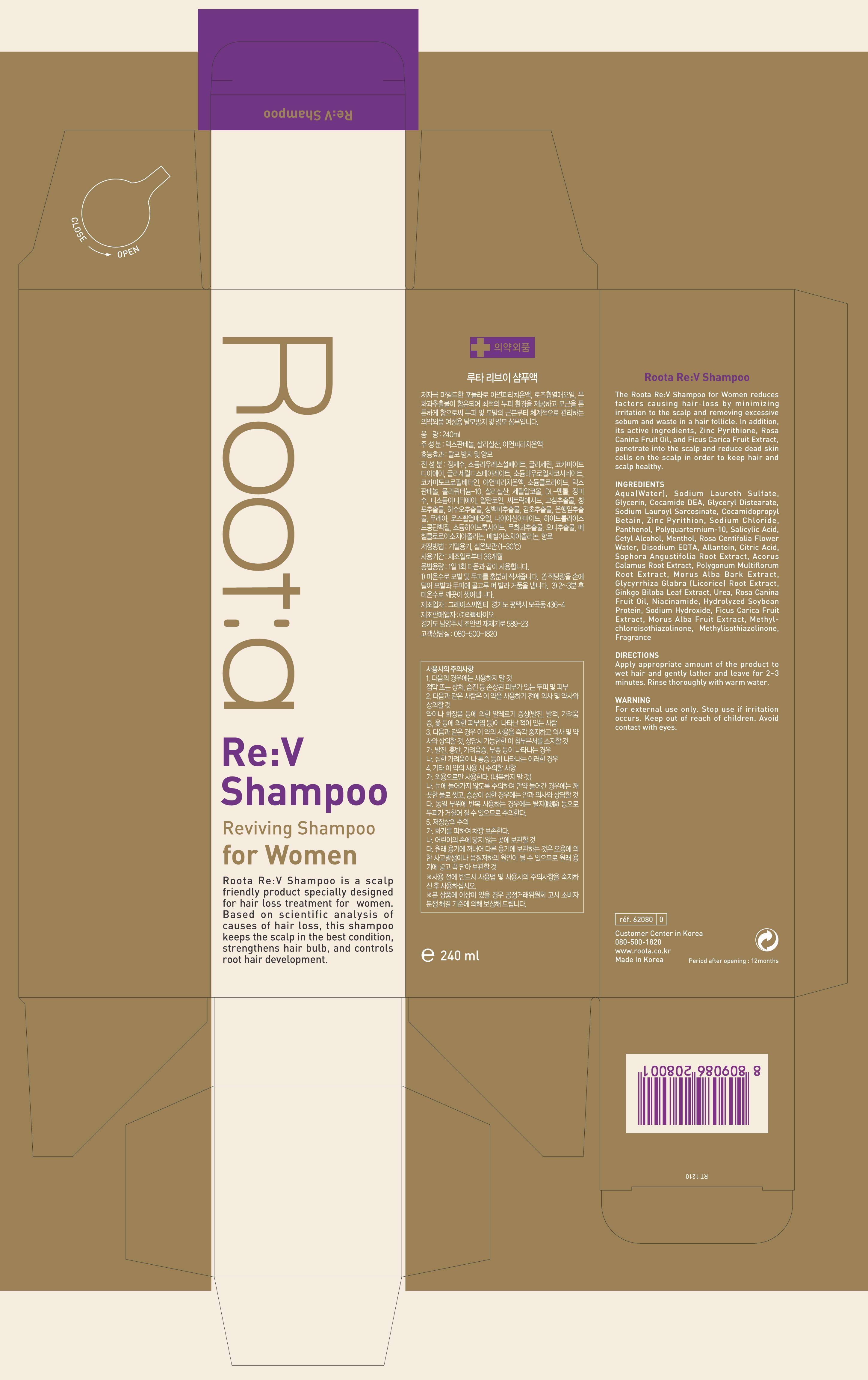 DRUG LABEL: Roota Re V for women
NDC: 54576-2001 | Form: SHAMPOO
Manufacturer: Raphabio Inc
Category: otc | Type: HUMAN OTC DRUG LABEL
Date: 20121231

ACTIVE INGREDIENTS: PANTHENOL 1.2 mg/240 mL
INACTIVE INGREDIENTS: WATER; COCO DIETHANOLAMIDE; SODIUM LAUROYL SARCOSINATE; COCAMIDOPROPYL BETAINE; GLYCERIN; EDETATE SODIUM; PYRITHIONE ZINC; SODIUM CHLORIDE; SODIUM LAURETH SULFATE; GLYCERYL DISTEARATE; MENTHOL; ROSA CENTIFOLIA FLOWER OIL; SALICYLIC ACID; CETYL ALCOHOL; ALLANTOIN; CITRIC ACID MONOHYDRATE; SOPHORA FLAVESCENS ROOT; EDETATE DISODIUM; FALLOPIA MULTIFLORA ROOT; ROSA CANINA FRUIT OIL; SOY PROTEIN; ACORUS CALAMUS ROOT; FIG; MORUS ALBA BARK; GLYCYRRHIZA GLABRA; GINKGO; UREA; NIACINAMIDE; SODIUM HYDROXIDE; CLOVE; METHYLCHLOROISOTHIAZOLINONE; METHYLISOTHIAZOLINONE

Drug Facts

ACTIVE INGREDIENT

panthenol

INACTIVE INGREDIENT

Aqua (Water), Cocamide DEA, Sodium Lauroyl Sarcosinate, Cocamidopropyl Betain, Glycerin, Tetrasodium EDTA, Zinc Pyrithion, Sodium Chloride, Sodium laureth sulfate, Glyceryl Distearate, Menthol,Polyquarternium-10, Mentha Piperita (Peppermint) oil, Salicylic Acid,Cetyl Alcohol, Allantoin,Citric Acid,Zinc Sulfate,Disodium EDTA,Rosmarinus Officinalis (Rosemary) Leaf Oil, Pyridoxine HCl,Sophora Angustifolia Root Extract,Acorus Calamus Root Extract ,Polygonum Multiflorum Root Extract, Morus Alba Bark Extract, Glycyrrhiza Glabra (Licorice) Root Extract ,Ginkgo Biloba Leaf Extract, Urea,Niacinamide,Sodium Hydroxide,Copper Tripeptide-1,Methylchloroisothiazolinone, Methylisothiazolinone, cocamide DEA, Rosa centifolia flower water, sophora angustifolia root extract, polygonum multiflorum root extract, rosa canina fruit oil, hydrolyzed soybean protein, ficus carica fruit extract, fragrance

PURPOSE

hair care

keep out or reach of the children

INDICATIONS AND USAGE

1. apply sufficient quantity to intended part
2. scrub softly as like doing massage

stop use if irritation occurs

DOSAGE AND ADMINISTRATION

for external use only